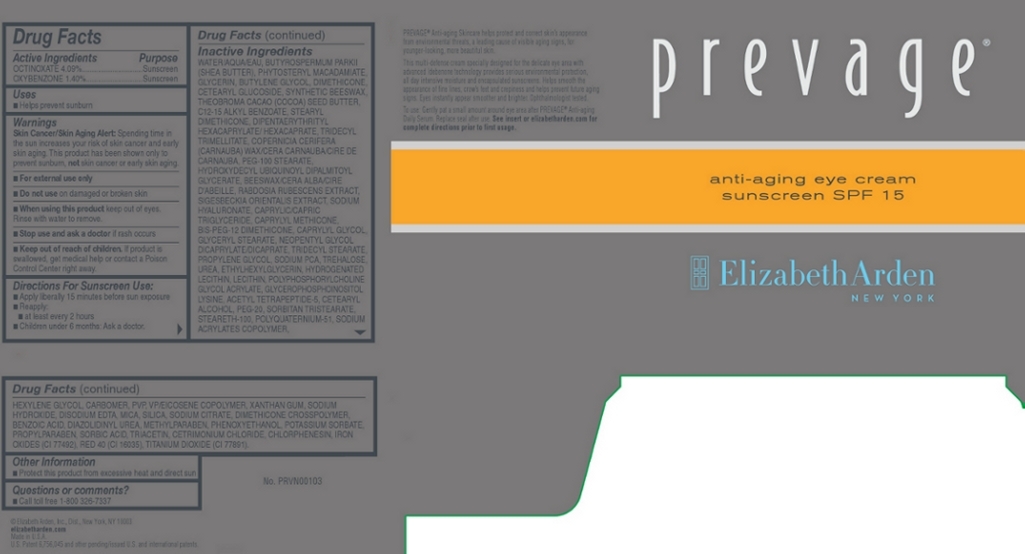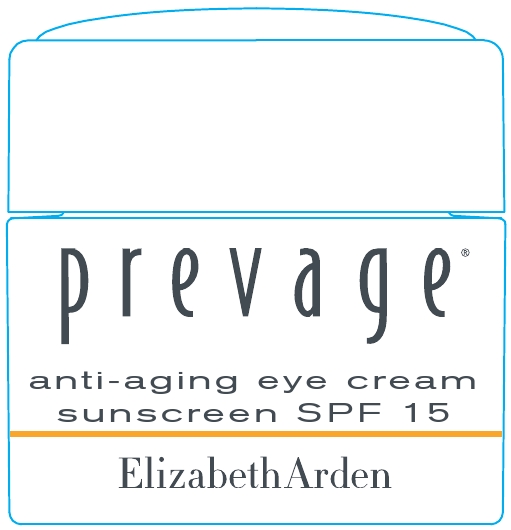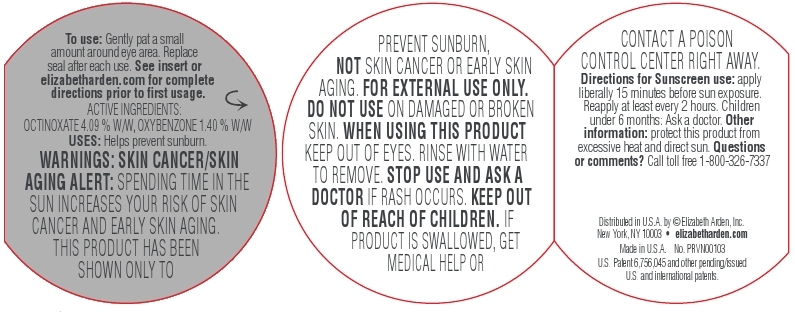 DRUG LABEL: Prevage Anti Aging Eye Sunscreen SPF 15
NDC: 67938-1126 | Form: CREAM
Manufacturer: Elizabeth Arden, Inc
Category: otc | Type: HUMAN OTC DRUG LABEL
Date: 20130426

ACTIVE INGREDIENTS: OCTINOXATE 0.613 g/15 g; OXYBENZONE 0.21 g/15 g
INACTIVE INGREDIENTS: WATER; SHEA BUTTER; GLYCERIN; BUTYLENE GLYCOL; DIMETHICONE; CETEARYL GLUCOSIDE; DIPENTAERYTHRITYL HEXACAPRYLATE/HEXACAPRATE; TRIDECYL TRIMELLITATE; CARNAUBA WAX; PEG-100 STEARATE; GLYCERYL MONOSTEARATE; PHENOXYETHANOL; MICA; MEDIUM-CHAIN TRIGLYCERIDES; SODIUM PYRROLIDONE CARBOXYLATE; TRIDECYL STEARATE; UREA; YELLOW WAX; POLYETHYLENE GLYCOL 1000; SORBITAN TRISTEARATE; STEARETH-100; CHLORPHENESIN; CAPRYLYL GLYCOL; PROPYLENE GLYCOL; BENZOIC ACID; CETOSTEARYL ALCOHOL; XANTHAN GUM; SODIUM HYDROXIDE; DIAZOLIDINYL UREA; TREHALOSE; EDETATE DISODIUM; HEXYLENE GLYCOL; SORBIC ACID; METHYLPARABEN; SILICON DIOXIDE; PROPYLPARABEN; POTASSIUM SORBATE; TRIACETIN; HYALURONATE SODIUM; CETRIMONIUM CHLORIDE; ETHYLHEXYLGLYCERIN; SODIUM CITRATE

BC1126

DESCRIPTION

PREVAGE Anti-aging Skincare helps protect and correct skin’s appearance from environmental threats, a leading cause of visible aging signs, for younger-looking, more beautiful skin. This multi-defense cream specially designed for the delicate eye area with advanced Idebenone technology provides serious environmental protection, all day intensive moisture and encapsulated sunscreens. Helps smooth the appearance of fine lines, crow’s feet and crepiness and helps prevent future aging signs. Eyes instantly appear smoother and brighter. Ophthalmologist tested.

INDICATIONS AND USAGE

To Use: Gently pat a small amount around eye area after PREVAGE Anti-aging Daily Serum.

Directions For Sunscreen Use: Apply liberally 15 minutes before sun exposure. Reapply at least every 2 hours. Children under 6 months: Ask a doctor.

WARNINGS

Skin Cancer/Skin Aging Alert: Spending time in the sun increases your risk of skin cancer and early skin aging. This product has been shown only to prevent sunburn, not skin cancer or early skin aging.

For external use only.

Do not use on damaged or broken skin.

When using this product keep out of eyes. Rinse with water to remove.

Stop use and ask a doctor if rash occurs

OTC - ACTIVE INGREDIENT

Active Ingredients: Octinoxate, 4.09%, Oxybenzone, 1.40%.

INACTIVE INGREDIENT

Other Ingredients: Water/Aqua/Eau, Butyrospermum Parkii (Shea Butter), Phytosteryl Macadamiate, Glycerin, Butylene Glycol, Dimethicone, Cetearyl Glucoside, Synthetic Beeswax, Theobroma Cacao (Cocoa) Seed Butter, C12-15 Alkyl Benzoate, Stearyl Dimethicone, Dipentaerythrityl Hexacaprylate/Hexacaprate, Tridecyl Trimellitate, Copernicia Cerifera (Canauba) Wax/Cera Carnauba/Cire De Carnauba, Peg-100 Stearate, Hydroxydecyl Ubiquinoyl Dipalmitoyl Glycerate, Beeswax/Cera Alba/Cire D'Abeille, Rabdosia Rubescens Extract, Sigesbeckia Orientalis Extract, Sodium Hyaluronate, Caprylic/Capric Triglyceride, Caprylyl Methicone, BIS-PEG-12 Dimethicone, Caprylyl Glycol, Glyceryl Stearate, Neopentyl Glycol Dicaprylate/Dicaprate, Tridecyl Stearate, Propylene Glycol, Sodium PCA, Trehalose, Urea, Ethylhexylglycerin, Hydrogenated Lecithin, Lecithin, Polyphosphorylcholine Glycol Acrylate, Glycerophosphoinositol Lysine, Acetyl Tetrapeptide-5, Cetearyl Alcohol, PEG-20, Sorbitan Tristearate, Steareth-100, Polyquaternium-51, Sodium Acrylates Copolymer, Hexylene Glycol, Carbomer, PVP, VP/Eicosene Copolymer, Xanthan Gum, Sodium Hydroxide, Disodium EDTA, Mica, Silica, Sodium Citrate, Dimethicone Crosspolymer, Benzoic Acid, Diazolidinyl Urea, Methyparaben, Phenoxyethanol, Potassium Sorbate, Propylparaben, Sorbic Acid, Triacetin, Cetrimonium Chloride, Chlorphenesis, Iron Oxides (CI 77492), Red 40 (CI 16035), Titanium Dioxide (CI 77891).

DOSAGE & ADMINISTRATION

Pat around eye area.

OTC - KEEP OUT OF REACH OF CHILDREN

Keep out of reach of children. If product is swallowed, get medical help or contact a Poison Control Center right away.

OTC - PURPOSE

Provides SPF 15 Sun Protection.

OTC - WHEN USING

Keep out of eyes.